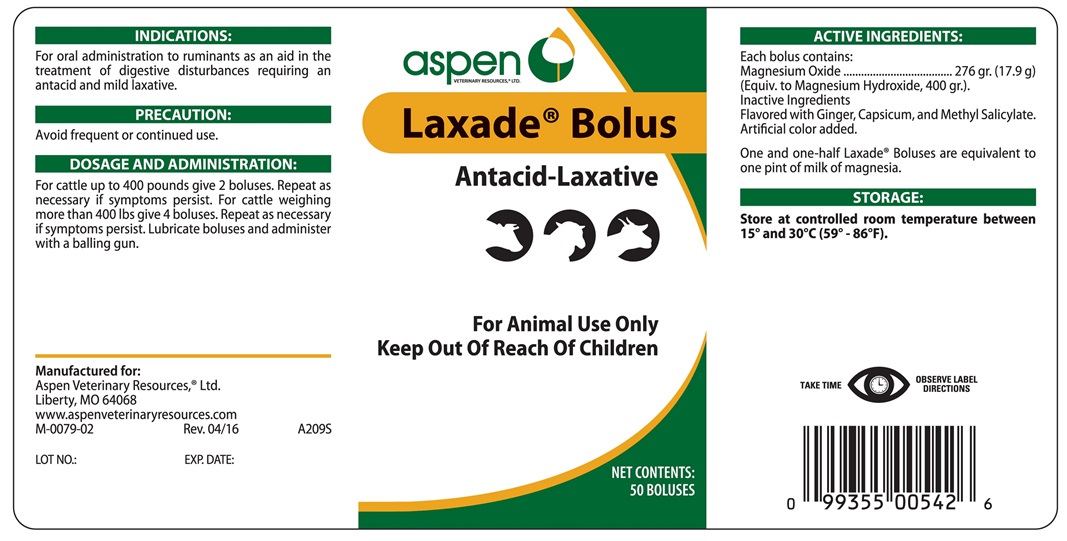 DRUG LABEL: LAXADE
NDC: 46066-264 | Form: TABLET
Manufacturer: Aspen Veterinary Resources, Ltd.
Category: animal | Type: OTC ANIMAL DRUG LABEL
Date: 20170523

ACTIVE INGREDIENTS: MAGNESIUM OXIDE 276 g/1 1

Laxade Bolus

INDICATIONS AND USAGE

Antacid-Laxative

For Animal Use Only

Keep Out of Reach of Children

INDICATIONS

For oral administration to ruminants as an aid in the treatment of digestive disturbances requiring an antacid and mild laxative.

PRECAUTIONS

Avoid frequent or continued use.

DOSAGE AND ADMINISTRATION

For cattle up to 400 pounds give 2 boluses. Repeat as necessary if symptoms persist. For cattle weighing more than 400 lbs give 4 boluses. Repeat as necessary if symptoms persist. Lubricate boluses and administer with a balling gun.

ACTIVE INGREDIENTS

Each bolus contains:

Magnesium Oxide .................................... 276 gr. (17.9 g)

(Equiv. to Magnesium Hydroxide, 400 gr.)

Inactive Ingredients

Flavored with Ginger, Capsicum, and Methyl Salicylate.

Artificial color added.

One and one-half Laxade Boluses are equivalent to one pint of milk of magnesia.

STORAGE

Store at controlled room temperature between 15° and 30°C (59°-86°F)

TAKE TIME OBSERVE LABEL DIRECTIONS